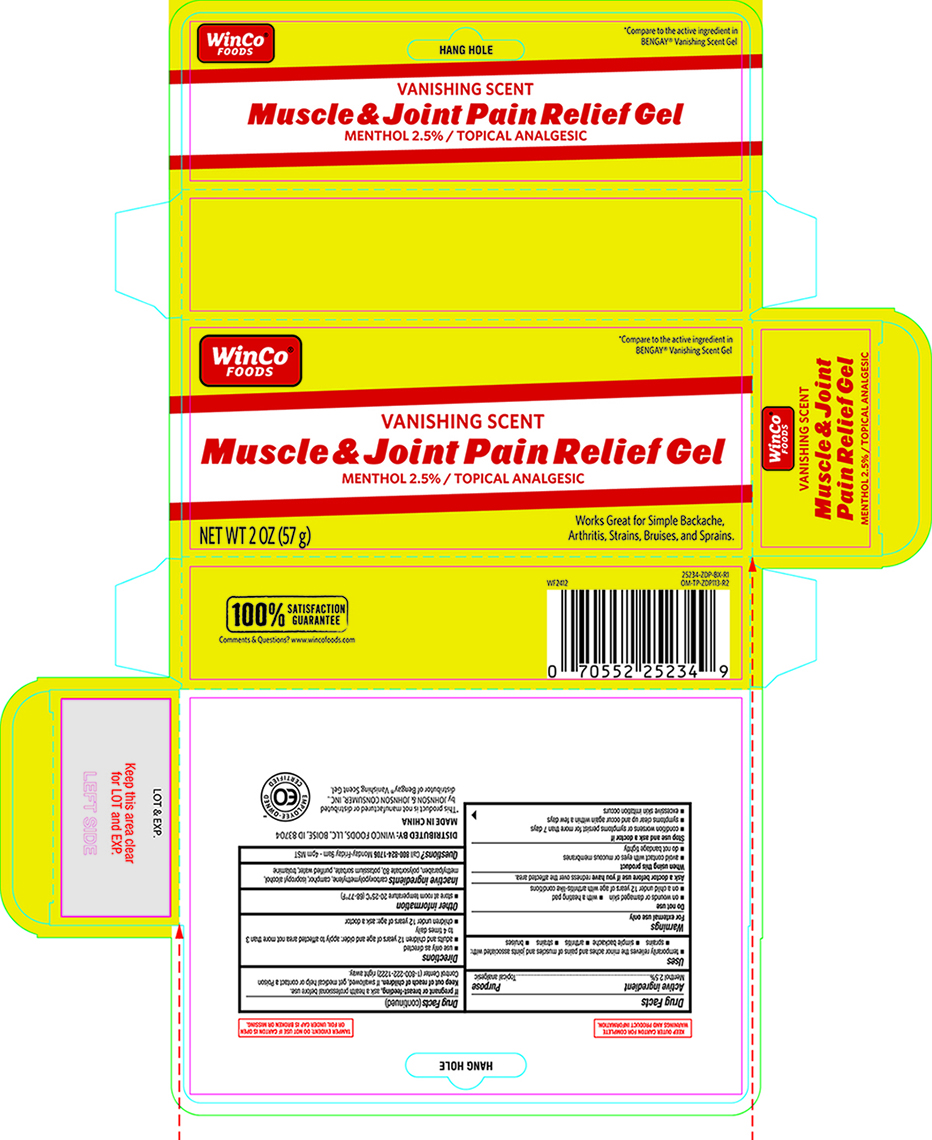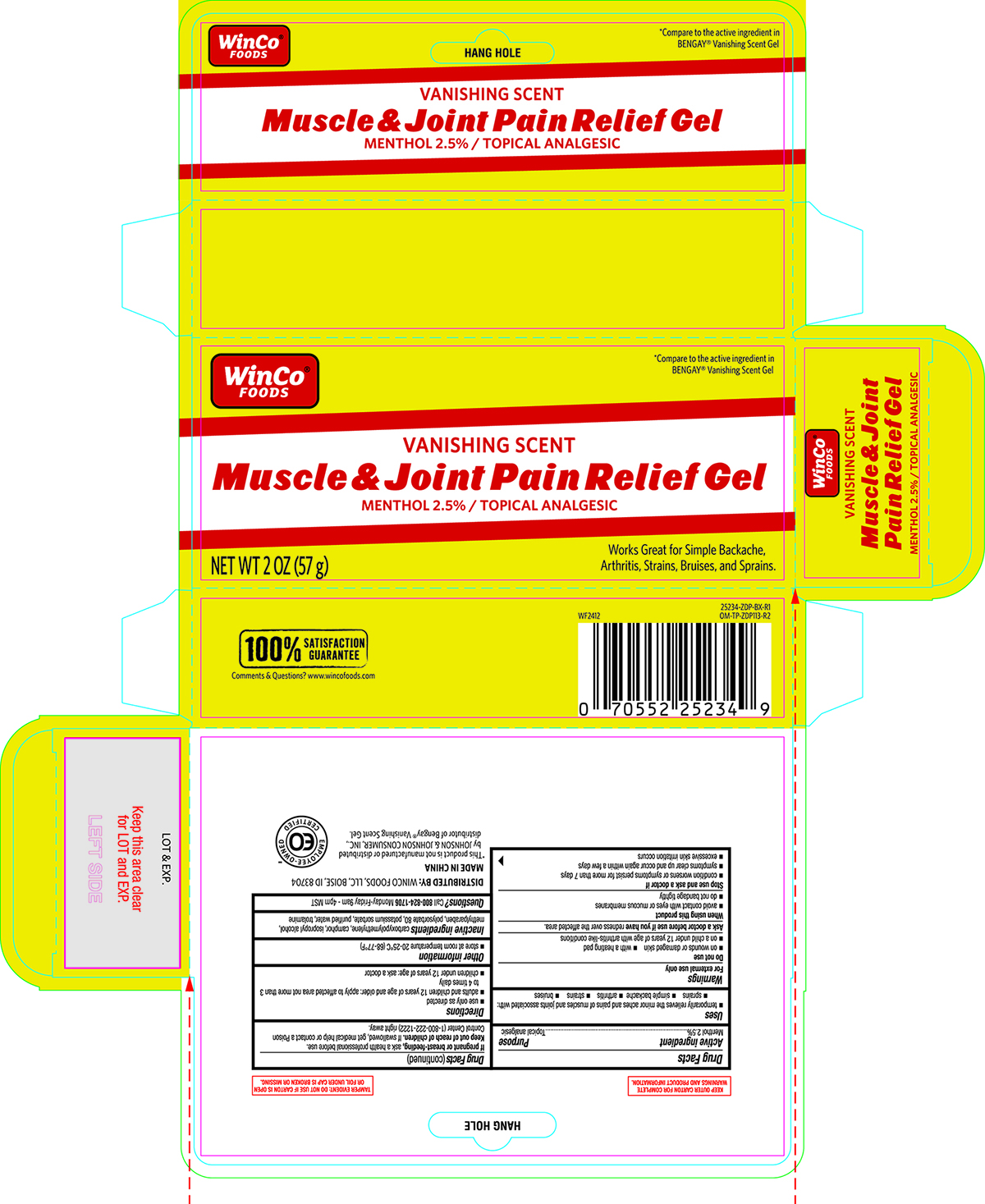 DRUG LABEL: Winco Muscle and Joint Pain Relief Gel 2oz
NDC: 67091-941 | Form: GEL
Manufacturer: WINCO FOODS, LLC
Category: otc | Type: HUMAN OTC DRUG LABEL
Date: 20260106

ACTIVE INGREDIENTS: MENTHOL 25 mg/1 g
INACTIVE INGREDIENTS: ISOPROPYL ALCOHOL; METHYLPARABEN; TROLAMINE; WATER; CAMPHOR (SYNTHETIC); CARBOMER; POTASSIUM SORBATE; POLYSORBATE 80

Winco Muscle & Joint 25234 Pain Relief Gel 2oz

Active ingredient Purpose
Menthol 2.5%.....................................................................................Topical analgesic

Uses
 temporarily relieves the minor aches and pains of muscles and joints associated with:
 sprains  simple backache  arthritis  strains  bruises

Warnings
For external use only

Do not use

 on wounds or damaged skin  with a heating pad

 on a child under 12 years of age with arthritis-like conditions

Ask a doctor before use if you have redness over the affected area.

When using this product
 avoid contact with eyes or mucous membranes
 do not bandage tightly

Stop use and ask a doctor if
 condition worsens or symptoms persist for more than 7 days
 symptoms clear up and occur again within a few days
 excessive skin irritation occurs

PREGNANCY OR BREAST FEEDING

If pregnant or breast-feeding, ask a health professional before use.

Keep out of reach of children. If swallowed, get medical help or contact a Poison
Control Center (1-800-222-1222) right away.

Directions
 use only as directed
 adults and children 12 years of age and older: apply to affected area not more than 3
to 4 times daily
 children under 12 years of age: ask a doctor

Other information
 store at room temperature 20-25°C (68-77°F)

Inactive ingredients carboxypolymethylene, camphor, isopropyl alcohol,
methylparaben, polysorbate 80, potassium sorbate, purified water, trolamine

Questions or comments?

Call 800-824-1706 Monday-Friday 9am - 4pm MST

Distributed By: WINCO FOODS, LLC, BOISE, ID 83704

Made in China